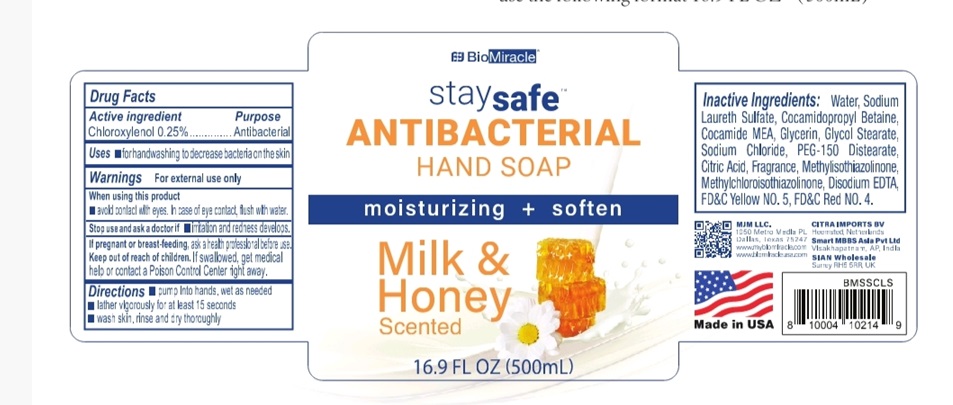 DRUG LABEL: BioMiracle staysafe ANTIBACTERIAL HANDSoap
NDC: 77978-525 | Form: LIQUID
Manufacturer: MJM SOURCING, LLC
Category: otc | Type: HUMAN OTC DRUG LABEL
Date: 20200527

ACTIVE INGREDIENTS: CHLOROXYLENOL 1.25 g/500 mL
INACTIVE INGREDIENTS: GLYCERIN; WATER; SODIUM LAURETH SULFATE; GLYCOL STEARATE; COCAMIDOPROPYL BETAINE; COCO MONOETHANOLAMIDE; METHYLISOTHIAZOLINONE; FD&C YELLOW NO. 5; FD&C RED NO. 4; SODIUM CHLORIDE; PEG-150 DISTEARATE; CITRIC ACID MONOHYDRATE; METHYLCHLOROISOTHIAZOLINONE; EDETATE DISODIUM

Labeler : MJM SOURCING, LLC
NDC : 77978-525-01
BioMiracle staysafe ANTIBACTERIAL HAND SOAP